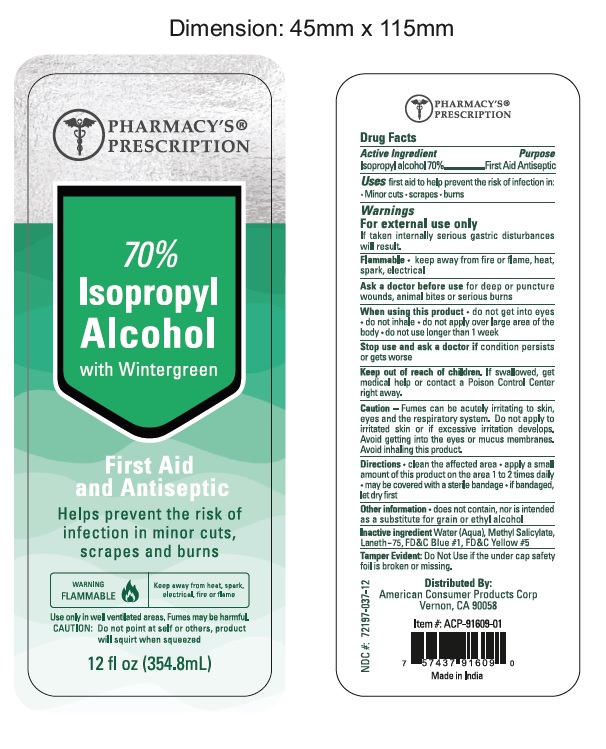 DRUG LABEL: PHARMACY PRESCRIPTION 70% ISOPROPYL ALCOHOL WITH WINTERGREEN
NDC: 68121-002 | Form: LIQUID
Manufacturer: PATCOS COSMETICS (INDIA) PRIVATE LIMITED
Category: otc | Type: HUMAN OTC DRUG LABEL
Date: 20201207

ACTIVE INGREDIENTS: ISOPROPYL ALCOHOL 70 mL/100 mL
INACTIVE INGREDIENTS: WATER; METHYL SALICYLATE; LANETH-75; FD&C BLUE NO. 1; FD&C YELLOW NO. 5

EXTRA INFORMATION ON FRONT LABEL :

- FIRST AID AND ANTISEPTIC: Helps prevent the risk of infection in minor cuts, scrapes and burns
- WARNING :Flammable,keep away from heat ,spark ,electrical fire or flame : Use only in well ventilated area .Fumes may be harmful
- CAUTION : Do not point at self or others, product will squirt when squeezed

Active Ingredients

Isopropyl Alcohol 70%

Purpose

First Aid Antiseptic

Uses

First aid to help prevent the risk of infection in

- Minor cuts
- Scrapes
- Burns

Warnings

For external use only

- If taken internally serious gastric disturbances will result.

Flammable : keep away from fire or flame ,heat, spark ,electrical.

Ask a doctor before use for deep or puncture wounds, animal bites or serious burns.

When using this product : do not get into eyes ,do not inhale ,do not apply over large area of the body ,do not use longer than 1 week.

Stop use and ask a doctor if condition persist or get worse.

Keep out of reach of children

If swallowed ,get medical help or contact a Poison Control Center right away.

Caution –

- Fumes can be acutely irritating to skin ,eyes and the respiratory system.
- Do not apply to irritated skin or if excessive irritation develops.
- Avoid getting into eyes or mucus membranes .Avoid inhaling this product.

Directions

- Clean the affected area.
- Apply a small amount of this product on the area 1 to 2 times daily.
- May be covered with a sterile bandage.
- If bandaged lets dry first.

Other Information

- Does not contain ,nor is intended as a substitute for grain or ethyl alcohol.
- Tamper Evident : Do not use if the under cap safety foil is broken or missing.

Inactive ingredients

- Water (Aqua)
- Methyl Salicylate
- Laneth -75
- FD and C Blue #1
- FD AND C YELLOW #5